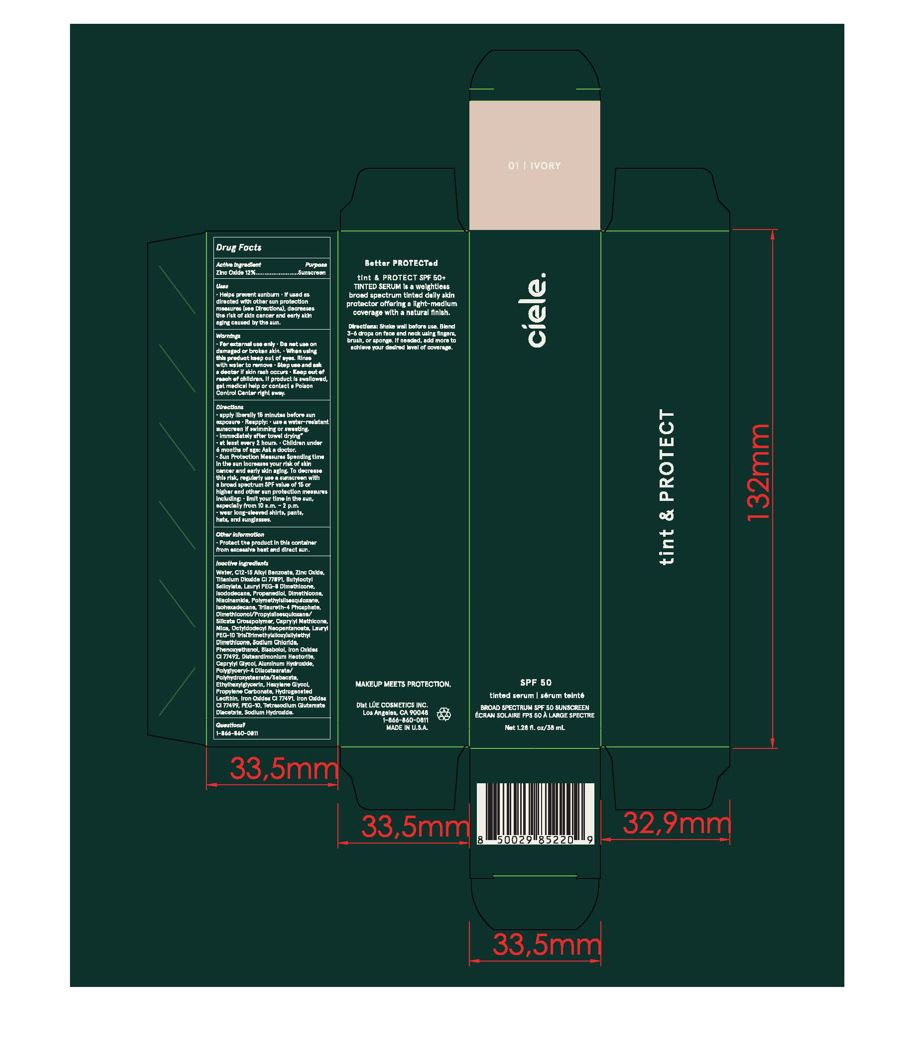 DRUG LABEL: Ciele Tint and Protect
NDC: 83103-1819 | Form: LOTION
Manufacturer: Ciele
Category: otc | Type: HUMAN OTC DRUG LABEL
Date: 20251015

ACTIVE INGREDIENTS: ZINC OXIDE 132 mg/1 mL
INACTIVE INGREDIENTS: ALKYL (C12-15) BENZOATE; TRILAURETH-4 PHOSPHATE; BUTYLOCTYL SALICYLATE; LAURYL PEG-8 DIMETHICONE (300 CPS); .ALPHA.-BISABOLOL, (+)-; FERRIC OXIDE YELLOW; WATER; NIACINAMIDE; PROPANEDIOL; TETRASODIUM GLUTAMATE DIACETATE; SODIUM CHLORIDE; POLYGLYCERYL-4 DIISOSTEARATE/POLYHYDROXYSTEARATE/SEBACATE; ETHYLHEXYLGLYCERIN; DISTEARDIMONIUM HECTORITE; CAPRYLYL GLYCOL; LECITHIN, SOYBEAN; ALLANTOIN; DIMETHICONE; PHENOXYETHANOL; SODIUM HYDROXIDE; PROPYLENE CARBONATE; HEXYLENE GLYCOL; MICA; FERRIC OXIDE RED; POLYMETHYLSILSESQUIOXANE (11 MICRONS); ISODODECANE; ISOHEXADECANE; DIMETHICONOL/PROPYLSILSESQUIOXANE/SILICATE CROSSPOLYMER (450000000 MW); OCTYLDODECYL NEOPENTANOATE

Ciele Tint and Protect